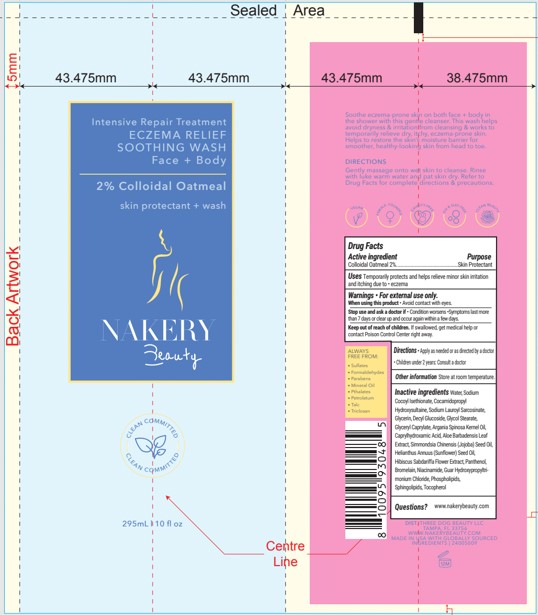 DRUG LABEL: ECZEMA RELIEF SOOTHING WASH
NDC: 83092-104 | Form: GEL
Manufacturer: Three Dog Beauty LLC
Category: otc | Type: HUMAN OTC DRUG LABEL
Date: 20221103

ACTIVE INGREDIENTS: OATMEAL 2 g/100 mL
INACTIVE INGREDIENTS: GLYCERYL CAPRYLATE; ARGAN OIL; CAPRYLHYDROXAMIC ACID; PANTHENOL; BROMELAINS; SOY SPHINGOLIPIDS; EGG PHOSPHOLIPIDS; NIACINAMIDE; GLYCOL STEARATE; ALOE VERA LEAF; SUNFLOWER OIL; GUAR HYDROXYPROPYLTRIMONIUM CHLORIDE (1.7 SUBSTITUENTS PER SACCHARIDE); TOCOPHEROL; DECYL GLUCOSIDE; JOJOBA OIL; HIBISCUS SABDARIFFA FLOWER; GLYCERIN; WATER; SODIUM COCOYL ISETHIONATE; COCAMIDOPROPYL HYDROXYSULTAINE; SODIUM LAURYL SARCOSINATE

THREE DOG BEAUTY - NAKERY BEAUTY - ECZEMA RELIEF SOOTHING WASH (83092-104)

ACTIVE INGREDIENT

COLLOIDAL OATMEAL 2%

PURPOSE

SKIN PROTECTANT

USES

TEMPORARILY PROTECTS AND HELPS RELIEVE MINOR SKIN IRRITATION AND ITCHING DUE TO ECZEMA.

WARNINGS

- FOR EXTERNAL USE ONLY.

WHEN USING THIS PRODUCT

- AVOID CONTACT WITH EYES.

STOP USE AND ASK A DOCTOR IF

- CONDITION WORSENS
- SYMPTOMS LAST MORE THAN 7 DAYS OR CLEAR UP AND OCCUR AGAIN WITHIN A FEW DAYS.

KEEP OUT OF REACH OF CHILDREN. IF SWALLOWED, GET MEDICAL HELP OR CONTACT POISON CONTROL CENTER RIGHT AWAY.

DIRECTIONS

- APPLY AS NEEDED OR AS DIRECTED BY A DOCTOR.
- CHILDREN UNDER 2 YEARS: CONSULT A DOCTOR

OTHER INFORMATION

STORE AT ROOM TEMPERATURE.

INACTIVE INGREDIENTS

WATER, SODIUM COCOYL ISETHIONATE, COCAMIDOPROPYL HYDROXYSULTAINE, SODIUM LAURYL SARCOSINATE, GLYCERIN, DECYL GLUCOSIDE, GLYCOL STEARATE, GLYCERYL CAPRYLATE, ARGANIA SPINOSA KERNEL OIL, CAPRYLHYDROXAMIC ACID, ALOE BARBADENSIS LEAF EXTRACT, SIMMONDSIA CHINENSIS (JOJOBA) SEED OIL, HELIANTHUS ANNUUS (SUNFLOWER) SEED OIL, HIBISCUS SABDARIFFA FLOWER EXTRACT, PANTHENOL, BROMELAIN, NIACINAMIDE, GUAR HYDROXYPROPYLTRIMONIUM CHLORIDE, PHOSPHOLIPIDS, SPHINGOLIPIDS, TOCOPHEROL

QUESTIONS?

WWW.NAKERYBEAUTY.COM